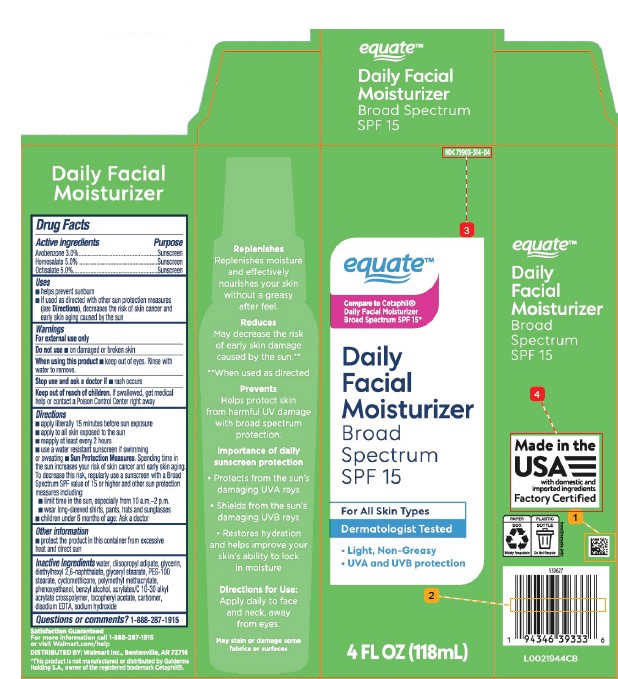 DRUG LABEL: Facial Moisturizer
NDC: 79903-314 | Form: LOTION
Manufacturer: Walmart Inc.
Category: otc | Type: HUMAN OTC DRUG LABEL
Date: 20260227

ACTIVE INGREDIENTS: AVOBENZONE 30 mg/1 mL; HOMOSALATE 50 mg/1 mL; OCTISALATE 50 mg/1 mL
INACTIVE INGREDIENTS: WATER; DIISOPROPYL ADIPATE; GLYCERIN; DIETHYLHEXYL 2,6-NAPHTHALATE; GLYCERYL MONOSTEARATE; PEG-100 MONOSTEARATE; CYCLOMETHICONE; POLY(METHYL METHACRYLATE; 450000 MW); PHENOXYETHANOL; BENZYL ALCOHOL; ACRYLATES/C10-30 ALKYL ACRYLATE CROSSPOLYMER (60000 MPA.S); .ALPHA.-TOCOPHEROL ACETATE; CARBOMER HOMOPOLYMER, UNSPECIFIED TYPE; EDETATE DISODIUM; SODIUM HYDROXIDE

Equate 195.000/195AB
Daily Facial Moisturizer SPF 15

Claim

DAILY FACIAL MOISTURIZER

Active Ingredients

Avobenzone 3.0%
Homosalate 5.0%
Octisalate 5.0%

Purpose

Sunscreen

Uses

- helps prevent sunburn
- if used as directed, with other sun protection measures (see Directions), decreases the risk of skin cancer and early skin aging caused by the sun

Warnings

For external use only

Do not use

- on damaged or broken skin

When using this product

- keep out of eyes. Rinse with water to remove.

Stop use and ask a doctor if

- rash occurs

Keep out of reach of children.

If swallowed, get medical help or contact a Poison Control Center right away.

Directions

- apply liberally 15 minutes before sun exposure
- apply to all skin exposed to the sun
- reapply at least every 2 hours
- use a water resistant sunscreen if swimming or sweating
- Sun Protection Measures. Spending time in the sun increases your risk of skin cancer and early skin aging. To decrease this risk, regularly use a sunscreen with a Broad Spectrum SPF value of 15 or higher and other sun protection measures including:
- limit time in the sun, especially from 10 a.m.–2 p.m.
- wear long-sleeved shirts, pants, hats and sunglasses
- children under 6 months of age: Ask a doctor

Other information

- protect the product in this container from excessive heat and direct sun

Inactive ingredients

water, diisopropyl adipate, glycerin, diethylhexyl 2,6-naphthalate, glyceryl stearate, PEG-100 stearate, cyclomethicone, polymethyl methacrylate, phenoxyethanol, benzyl alcohol, acrylates/C 10-30 alkyl acrylate crosspolymer, tocopheryl acetate, carbomer, disodium EDTA, sodium hydroxide

Questions or comments?

1-888-287-1915

Claims

equate

Daily Facial Moisturizer

Broad Spectrum SPF 15

Replenishes

Replenishes moisture and effectively nourishes your skin without a greasy after feel.

Reduces

May decrease the risk of early skin damage caused by the sun.**

**When used as directed

Prevents

Helps protect skin from harmful UV damage with broad spectrum protection.

Importance of daily sunscreen protection

- Protects from the sun's damaging UVA rays
- Shields from the sun's damaging UVB rays
- Restores hydration and helps improve your skin's ability to lock in moisture

Directions for Use:

Apply daily to face and neck, away from eyes.

May stain or damage some fabrics or surfaces

Adverse Reactions

Made in the USA with domestic and imported ingredients

Factory Certified

PAPER BOX

Widely Recyclable

PLASTIC BOTTLE

Do Not Recycle

how2recycle.info

Satisfaction guaranteed

For more information call 1-888-287-1915 or visit Walmart.com/help

DISTRIBUTED BY: Walmart Inc., Bentonville, AR 72716

Disclaimer

*This product is not manufactured or distributed by Galderma Holding S.A., owner of the registered trademark Cetaphil.

PRINCIPAL DISPLAY PANEL

NDC 79903-314-04

equate™

Compare to Cetaphil® Daily Facial Moisturizer Broad Spectrum SPF 15*

DAILY FACIAL MOISTURIZER

Broad Spectrum SPF 15 Sunscreen

For All Skin Types

Dermatologist Tested

- Light, Non-Greasy
- UVA and UVB protection

4 FL OZ (118 mL)